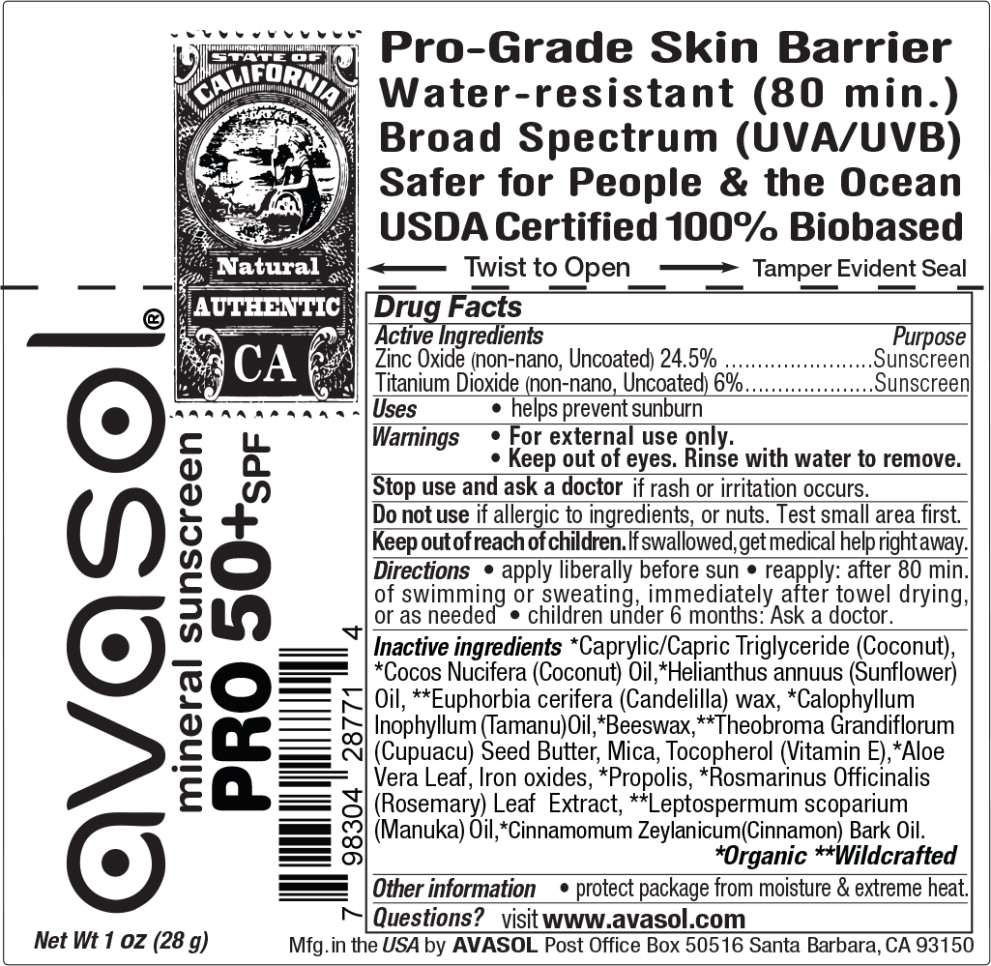 DRUG LABEL: Pro Formula
NDC: 58518-030 | Form: STICK
Manufacturer: Avasol LLC
Category: otc | Type: HUMAN OTC DRUG LABEL
Date: 20230424

ACTIVE INGREDIENTS: ZINC OXIDE 24.5 g/100 g; TITANIUM DIOXIDE 6 g/100 g
INACTIVE INGREDIENTS: MEDIUM-CHAIN TRIGLYCERIDES; COCONUT OIL; SUNFLOWER OIL; YELLOW WAX; TAMANU OIL; CANDELILLA WAX; THEOBROMA GRANDIFLORUM SEED; MICA; TOCOPHEROL; FERROUS OXIDE; PROPOLIS WAX; ALOE VERA LEAF; MANUKA OIL; ROSEMARY; CINNAMON BARK OIL

Drug Facts

Active Ingredients

Zinc Oxide (non-nano, Uncoated) 24.5%

Titanium Dioxide (non-nano, Uncoated) 6%

Purpose

Sunscreen

Sunscreen

Uses

- helps prevent sunburn

Warnings

- For external use only.
- Keep out of eyes. Rinse with water to remove.

Stop use and ask a doctor if rash or irritation occurs.

Do not use if allergic to ingredients, or nuts. Test small area first.

Keep out of reach of children. If swallowed, get medical help right away.

Directions

- apply liberally before sun
- reapply: after 80 min. of swimming or sweating, immediately after towel drying, or as needed
- children under 6 months: Ask a doctor.

Inactive ingredients

*Caprylic/Capric Triglyceride (Coconut), *Cocos Nucifera (Coconut) Oil,*Helianthus annuus (Sunflower) Oil, **Euphorbia cerifera (Candelilla) wax, *Calophyllum Inophyllum (Tamanu)Oil,*Beeswax,**Theobroma Grandiflorum (Cupuacu) Seed Butter, Mica, Tocopherol (Vitamin E),*Aloe Vera Leaf, Iron oxides, *Propolis, *Rosmarinus Officinalis (Rosemary) Leaf Extract, **Leptospermum scoparium (Manuka) Oil,*Cinnamomum Zeylanicum(Cinnamon) Bark Oil.

*Organic **Wildcrafted

Other information

- protect package from moisture & extreme heat.

Questions?

visit www.avasol.com

Principal Display Panel - 28 g Tube Label

avasol®

mineral sunscreen
PRO 50+SPF

Net Wt 1 oz (28 g)

Pro-Grade Skin Barrier

Water-resistant (80 min.)

Broad Spectrum (UVA/UVB)

Safer for People & the Ocean

USDA Certified 100% Biobased